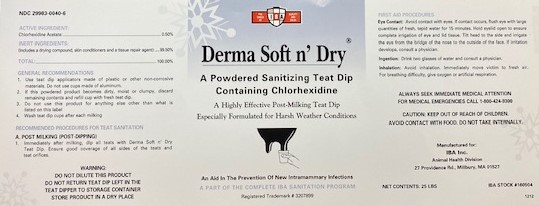 DRUG LABEL: DERMA SOFT N DRY
NDC: 29983-0040 | Form: POWDER
Manufacturer: IBA
Category: animal | Type: OTC ANIMAL DRUG LABEL
Date: 20220719

ACTIVE INGREDIENTS: CHLORHEXIDINE ACETATE .5 g/100 g

DERMA SOFT N' DRY A POWDERED SANITIZING TEAT DIP CONTAINING CHLORHEXIDINE A Highly Effective Post-Milking Teat Dip Especially Formulated for Harsh Weather Conditions An Aid in the prevention of New Intramammary Infections A PART OF THE COMPLETE IBA SANITATION PROGRAM

ACTIVE INGREDIENT:

Chlorhexidine Acetate:..........................................................0.50%

INERT INGREDIENTS:
(Includes a drying compound, skin conditioners and a tissue repair agent):......................99.50%

TOTAL........................................................................................................................................100%

INDICATIONS AND USAGE

GENERAL RECOMMENDATIONS
1. Use teat dip applicators made of plastic or other non-corrosive materials. Do not use cups made of aluminum.
2. If this powder becomes dirty and/or noticeably loses color, discard remaining contents and refill cup with fresh teat dip.
3. Do not use this product for anything else other than what is listed on this label.
4. Wash Teat Dip cups after each milking.

POST MILKING (POST -DIPPING)
1. Immediately after milking, dip all teats in Derma Soft n' Dry Teat Dip. Ensure good coverage of all sides of the teats and teat orifices.

WARNING

DO NOT DILUTE THIS PRODUCT
DO NOT RETURN TEAT DIP LEFT IN THE TEAT DIPPER TO STORAGE CONTAINER
STORE IN A DRY PLACE

CAUTION: KEEP OUT OF REACH OF CHILDREN. AVOID CONTACT WITH FOOD. DO NOT TAKE INTERNALLY.

FIRST AID PROCEDURES

EYE CONTACT: AVOID CONTACT WITH EYES. IF CONTACT OCCURS,FLUSH EYE WITH LARGE AMOUNTS OF FRESH, TEPID WATER FOR 15 MINUTES. HOLD EYELID OPEN TO ENSURE COMPLETE IRRIGATION OF EYE AND LID TISSUES. TILT HEAD TO THE SIDE AND IRRIGATE THE EYE FROM THE BRIDGE OF THE NOSE TO THE OUTSIDE OF THE FACE. IF IRRITATION DEVELOPS, CONSULT A PHYSICIAN.

INGESTION: DRINK TWO GLASSES OF WATER AND CONSULT A PHYSICIAN.

INHALATION: AVOID INHALATION. IMMEDIATELY MOVE VICTIM TO FRESH AIR. FOR BREATHING DIFFICULTY, GIVE OXYGEN OR ARTIFICIAL RESPIRATION.

ALWAYS SEEK IMMEDIATE MEDICAL ATTENTION

FOR MEDICAL EMERGENCIES CALL 1-800-424-9300